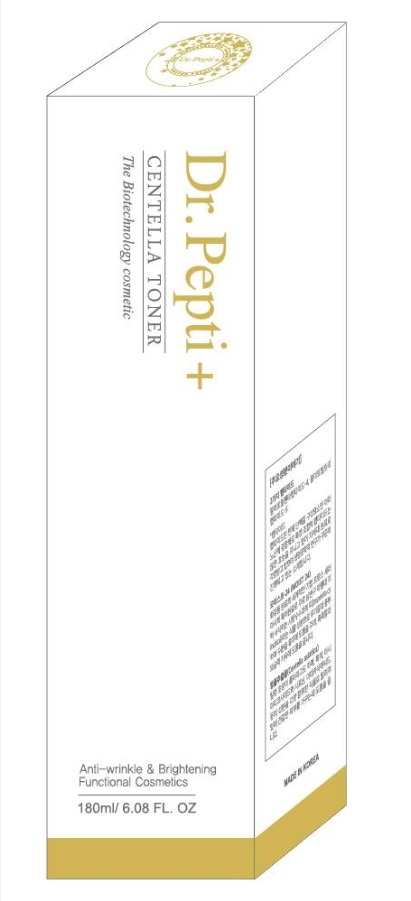 DRUG LABEL: Dr. Pepti CENTELLA TONER
NDC: 71146-0001 | Form: LIQUID
Manufacturer: J&COCEU Co Ltd
Category: otc | Type: HUMAN OTC DRUG LABEL
Date: 20161218

ACTIVE INGREDIENTS: NIACINAMIDE 2 g/100 mL; ADENOSINE 0.04 g/100 mL
INACTIVE INGREDIENTS: WATER; BUTYLENE GLYCOL; GLYCERIN

Drug Facts

ACTIVE INGREDIENT

Niacinamide, Adenosine

INACTIVE INGREDIENT

Glycerin, Water, Butylene Glycol, Betaine, Allantoin, Sodium Hyaluronate, etc.

PURPOSE

whitening
anti wrinkle

keep out of reach of the children

INDICATIONS AND USAGE

After wash one’s face, place desired amount into facial cotton pads, absorb softly following the skin texture.

WARNINGS

For external use only. Avoid contact with eyes and mouth.

Discontinue use if signs of irritation or rash appear.

Keep out of reach of children. Replace the cap after use.

DOSAGE AND ADMINISTRATION

for external use only